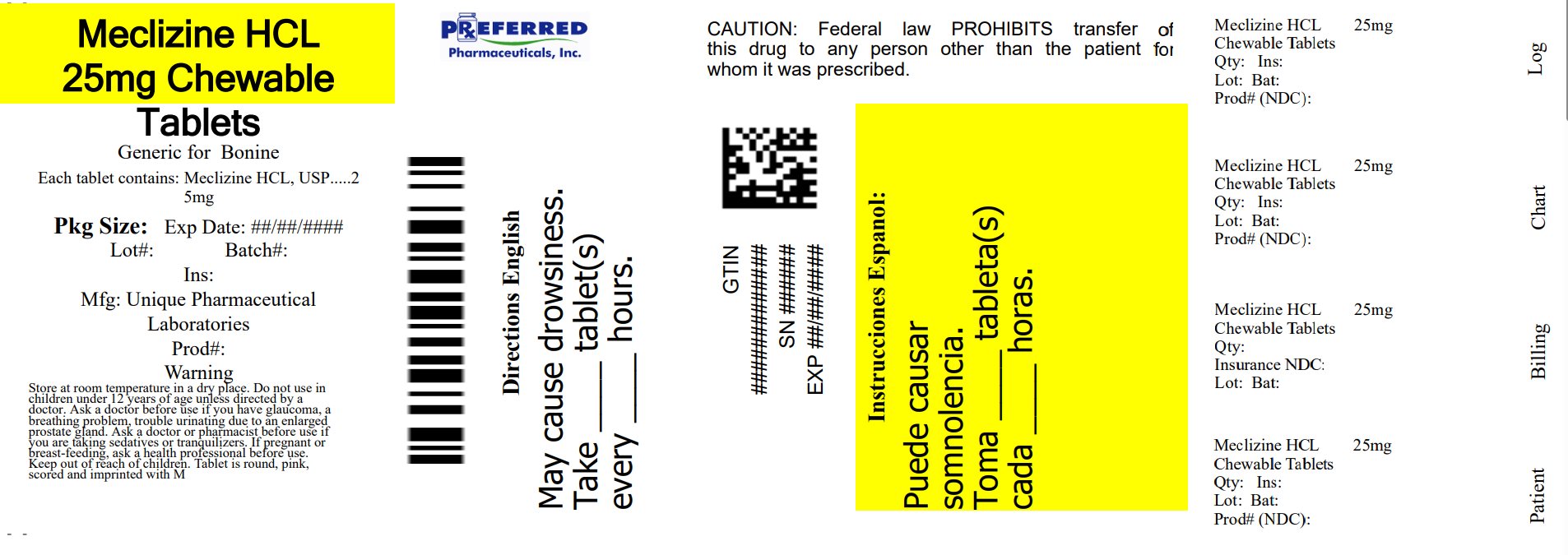 DRUG LABEL: Meclizine HCl
NDC: 68788-8529 | Form: TABLET, CHEWABLE
Manufacturer: Preferred Pharmaceuticals Inc.
Category: otc | Type: HUMAN OTC DRUG LABEL
Date: 20250805

ACTIVE INGREDIENTS: MECLIZINE HYDROCHLORIDE 25 mg/1 1
INACTIVE INGREDIENTS: ASPARTAME; CROSCARMELLOSE SODIUM; DEXTROSE, UNSPECIFIED FORM; FD&C RED NO. 40; MAGNESIUM STEARATE; MALTODEXTRIN; MICROCRYSTALLINE CELLULOSE; RASPBERRY; SILICON DIOXIDE; SODIUM SULFATE ANHYDROUS; SUCROSE; TRIBASIC CALCIUM PHOSPHATE

Meclizine Hydrochloride Chewable Tablets 25 mg

Drug Facts Active ingredient (in each chewable tablet)

Meclizine HCl, USP 25 mg

Purpose

Antiemetic

Uses

prevents and treats nausea, vomiting or dizziness due to motion sickness.

Warnings

Do not use in children under 12 years of age unless directed by a doctor

Ask a doctor before use if you have

- glaucoma
- a breathing problem such as emphysema or chronic bronchitis
- trouble urinating due to an enlarged prostate gland

Ask a doctor or pharmacist before use if you are taking sedatives or tranquilizers.

When using this product

- may cause drowsiness
- alcohol, sedatives, and tranquilizers may increase drowsiness
- avoid alcoholic drinks
- use caution when driving a motor vehicle or operating machinery

PREGNANCY OR BREAST FEEDING

If pregnant or breast-feeding, ask a health professional before use.

Keep out of reach of children.

In case of overdose, get medical help or contact the Poison Control Center immediately.

Directions

- Dosage should be taken one hour before travel starts
- Adults and children 12 years and older: Chew 1-2 tablets once daily, or as directed by a doctor
- Children under 12 years: do not give this product to children under 12 years of age unless directed by a doctor

Other Information

- Phenylketonurics: Contains Phenylalanine 0.0025 mg per tablet
- Store at room temperature in a dry place
- Keep lid tightly closed

Inactive ingredients

aspartame, colloidal silicon dioxide, croscarmellose sodium, dextrose, lake of FD & C Red 40, magnesium stearate, maltodextrin, microcrystalline cellulose, raspberry flavor, sodium sulfate anhydrous, sucrose, tribasic calcium phosphate

Questions or comments?

Call 1-844-474-7464 Monday to Friday 8 AM - 5 PM ET

TAMPER EVIDENT: DO NOT USE IF FOIL SEAL UNDER CAP, PRINTED WITH"SEALED for YOUR PROTECTION" IS BROKEN OR MISSING. Rising Pharma Holdings, Inc. is not affiliated with the owner of the registered trademark Bonine® Manufactured by: Unique Pharmaceutical Laboratories (A Div. of J.B. Chemicals & Pharmaceuticals Ltd.), Mumbai 400 030, India Distributed by: Rising Pharma Holdings, Inc. East Brunswick, NJ 08816 Mfg. Lic. No.: G/1430 Feb 2022

Repackaged By: Preferred Pharmaceutical Inc.

PRINCIPAL DISPLAY PANEL - 25 mg Chewable Tablet Label

Meclizine Hydrochloride Chewable Tablets

25 mg

68788-8529